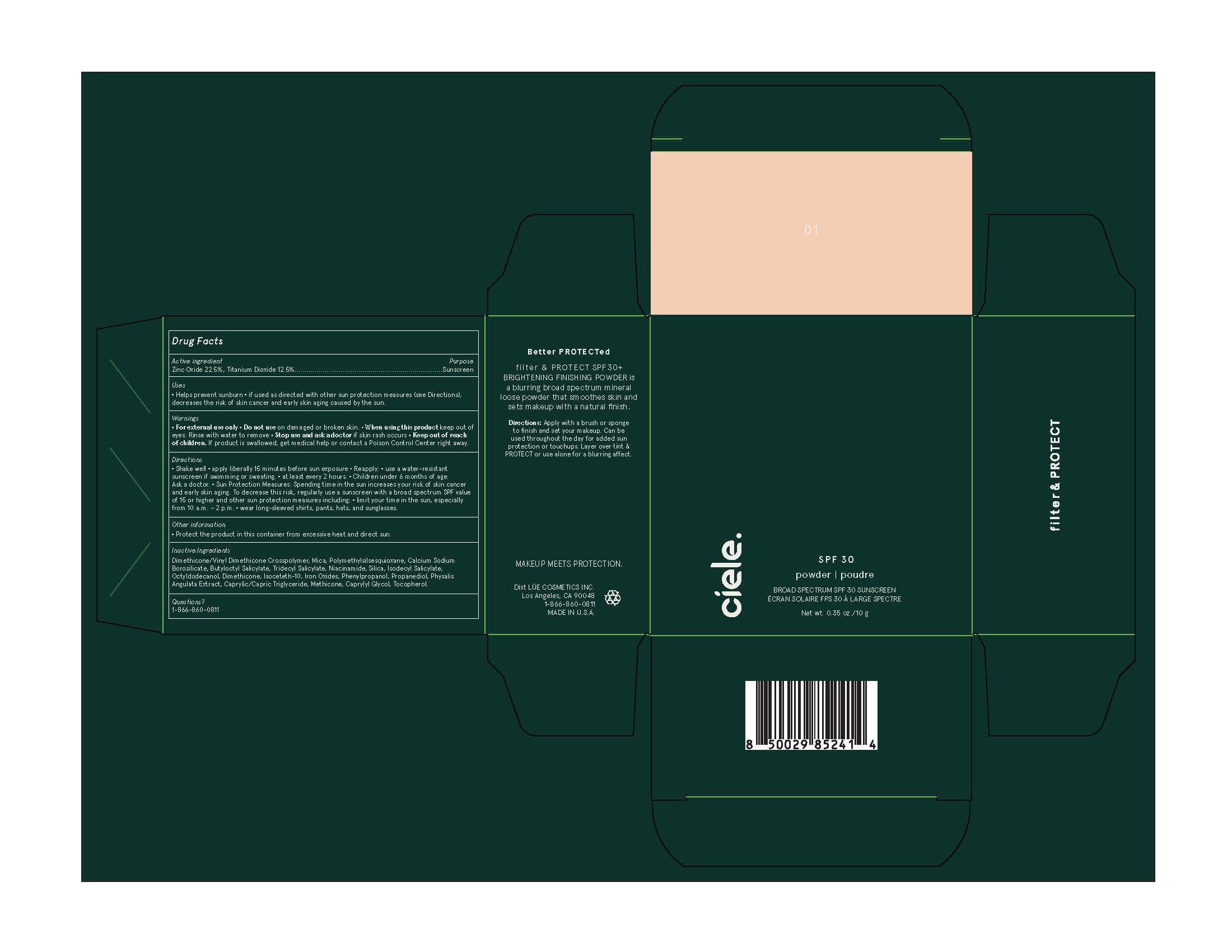 DRUG LABEL: Ciele Filter and Protect
NDC: 83103-1910 | Form: POWDER
Manufacturer: Ciele
Category: otc | Type: HUMAN OTC DRUG LABEL
Date: 20251015

ACTIVE INGREDIENTS: TITANIUM DIOXIDE 0.125 g/1 g; ZINC OXIDE 0.225 g/1 g
INACTIVE INGREDIENTS: POLYMETHYLSILSESQUIOXANE (11 MICRONS); DIMETHICONE/VINYL DIMETHICONE CROSSPOLYMER (SOFT PARTICLE); SILICON DIOXIDE; BUTYLOCTYL SALICYLATE; CAPRYLYL GLYCOL; PROPANEDIOL; PHYSALIS ANGULATA; NIACINAMIDE; TOCOPHEROL; TRIDECYL SALICYLATE; FERRIC OXIDE RED; MICA; ISODECYL SALICYLATE; DIMETHICONE; FERRIC OXIDE YELLOW; METHICONE (20 CST); ISOCETETH-10; OCTYLDODECANOL; PHENYLPROPANOL

Ciele Filter and Protect